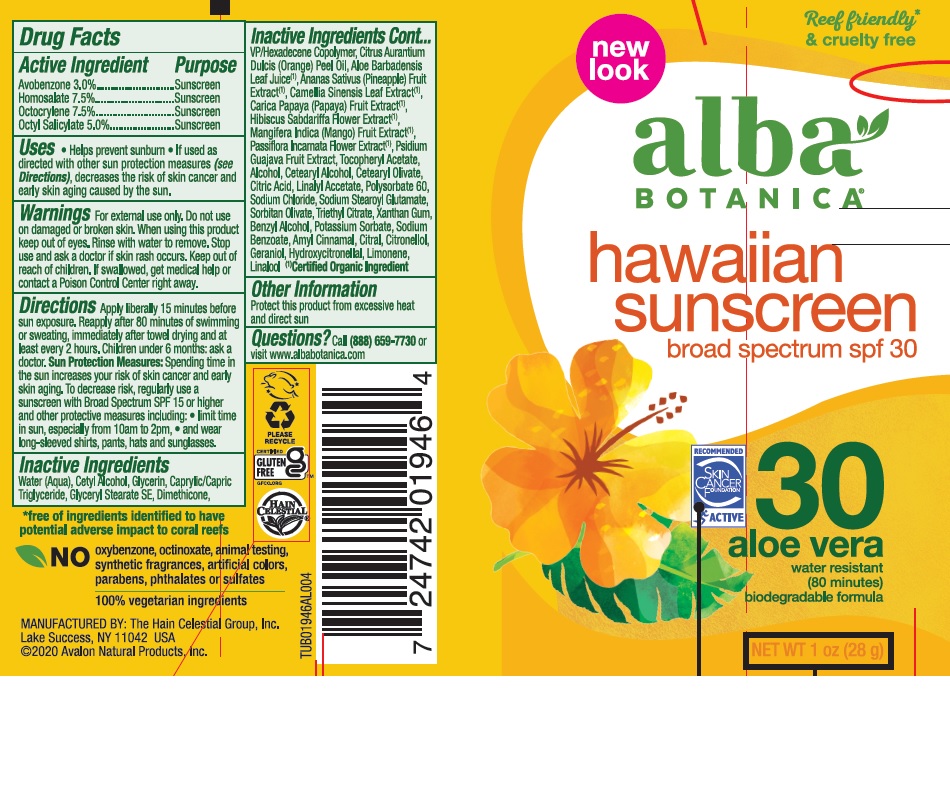 DRUG LABEL: Alba Botanica HW Sunscreen Aloe Vera SPF30
NDC: 61995-2008 | Form: LOTION
Manufacturer: The Hain Celestial Group, Inc.
Category: otc | Type: HUMAN OTC DRUG LABEL
Date: 20210412

ACTIVE INGREDIENTS: HOMOSALATE 7.5 g/100 g; OCTISALATE 5 g/100 g; OCTOCRYLENE 7.5 g/100 g; AVOBENZONE 3 g/100 g
INACTIVE INGREDIENTS: CITRUS AURANTIUM FRUIT OIL; LINALYL ACETATE; TRIETHYL CITRATE; MEDIUM-CHAIN TRIGLYCERIDES; CETEARYL OLIVATE; SODIUM CHLORIDE; SORBITAN OLIVATE; SODIUM BENZOATE; MANGO; PINEAPPLE; PAPAYA; HIBISCUS SABDARIFFA FLOWER; PASSIFLORA INCARNATA FLOWER; GUAVA; CITRIC ACID MONOHYDRATE; ALCOHOL; BENZYL ALCOHOL; ALOE VERA LEAF; GLYCERIN; WATER; VINYLPYRROLIDONE/HEXADECENE COPOLYMER; SODIUM STEAROYL GLUTAMATE; .ALPHA.-TOCOPHEROL ACETATE; GLYCERYL STEARATE SE; POTASSIUM SORBATE; CETYL ALCOHOL; DIMETHICONE; GREEN TEA LEAF; XANTHAN GUM; CETOSTEARYL ALCOHOL; POLYSORBATE 60

Alba Botanica HW Sunscreen Aloe Vera SPF30

Active Ingredient

Avobenzone - 3.0%

Homosalate - 7.5%

Octocrylene - 7.5%

Octyl Salicylate - 5.0%

DOSAGE AND ADMINISTRATION

Apply liberally 15 minutes before sun exposure. Reapply after 80 minutes of swimming or sweating, immediately after towel drying and at least every 2 hours.

PURPOSE

Sunscreen

WARNINGS

For external use only. Do not use on damaged or broken skin. When using this product keep out of eyes. Rinse with water to remove. Stop use and ask a doctor if skin rash occurs.

Keep out of reach of children. If swallowed get medical help or contact Poison Center right away.

INACTIVE INGREDIENT

Water (Aqua)

Cetyl Alcohol

Glycerin

Caprylic/Capric Triglyceride

Glyceryl Stearate SE

Dimethicone

VP/Hexadecene Copolymer

Citrus Aurantium Dulcis (Orange) Peel Oil

Aloe Barbadensis Leaf Juice (1)

Ananas Sativus (Pineapple) Fruit Extract (1)

Camellia Sinensis Leaf Extract (1)

Carica Papaya (Papaya) Fruit Extract (1)

Hibiscus Sabdariffa Flower Extract (1)

Mangifera Indica (Mango) Fruit Extract (1)

Passiflora Incarnata Flower Extract (1)

Psidium Guajava Fruit Extract

Tocopheryl Acetate

Alcohol

Cetearyl Alcohol

Cetearyl Olivate

Citric Acid

Linalyl Acetate

Polysorbate 60

Sodium Chloride

Sodium Stearoyl Glutamate

Sorbitan Olivate

Triethyl Citrate

Xanthan Gum

Benzyl Alcohol

Potassium Sorbate

Sodium Benzoate

Amyl Cinnamal

Citral

Citronellol

Geraniol

Hydroxycitronellal

Limonene

Linalool

(1) Certified Organic Ingredient

INDICATIONS AND USAGE

Helps prevents sunburns. If used as directed with other sun protection measures, decreases risk of skin cancer and early skin aging caused by sun exposure. Skin Protection Measures: Spending time in the sun increases your risk of skin cancer and early skin aging. To decrease risk, regularly use sunscreen with Broad Spectrum SPF 15 or higher and other protective measures including: limit time in sun, especially from10am to 2pm, and wear long sleeved shirts, pants, hats and sunglases.